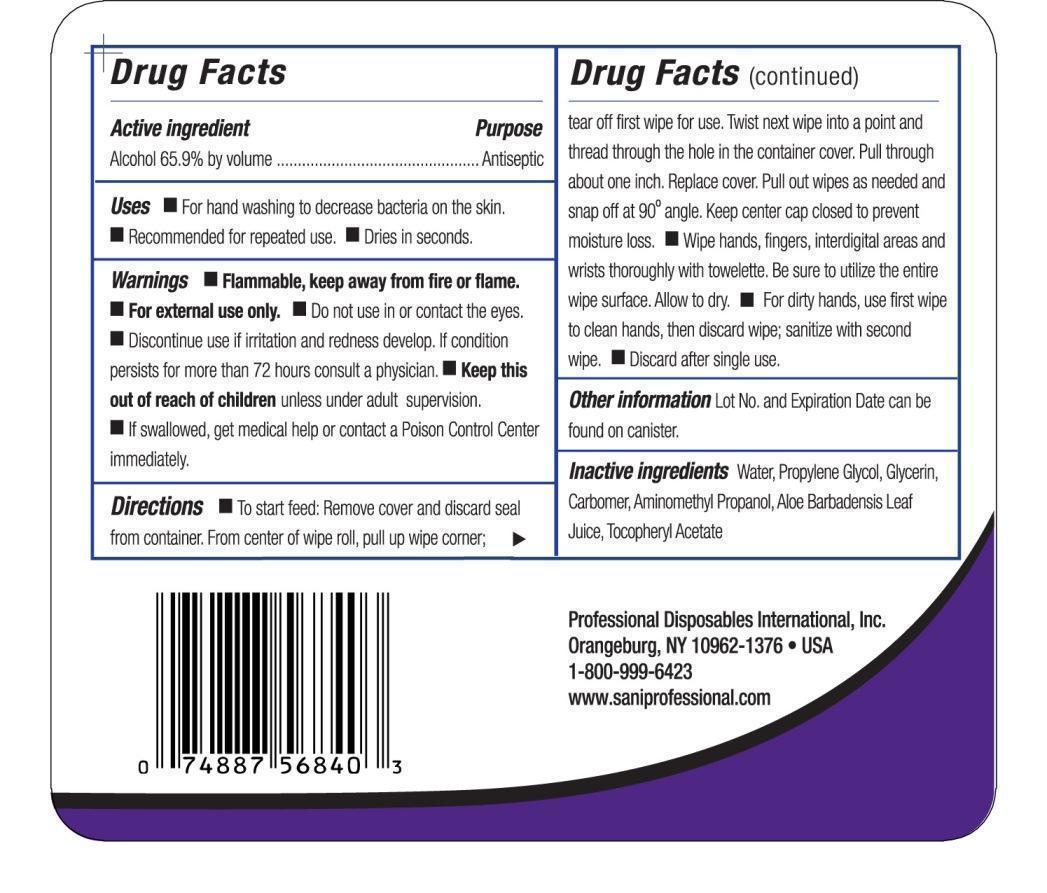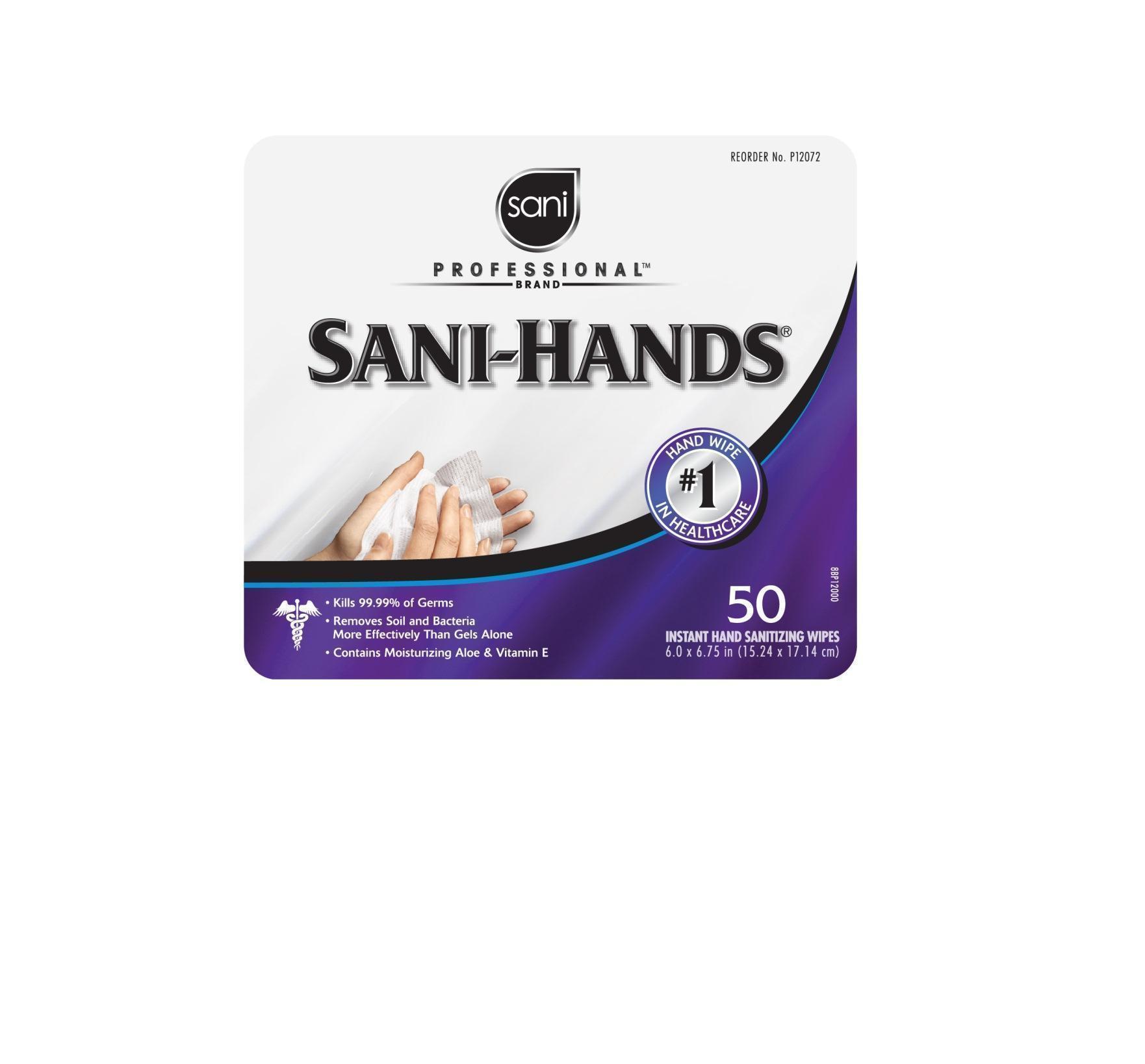 DRUG LABEL: Sani Professional Brand Sani-Hands
NDC: 10819-7003 | Form: CLOTH
Manufacturer: Profesional Disposables International, Inc.
Category: otc | Type: HUMAN OTC DRUG LABEL
Date: 20130228

ACTIVE INGREDIENTS: Alcohol 0.659 mL/1 mL
INACTIVE INGREDIENTS: WATER; PROPYLENE GLYCOL; GLYCERIN; CARBOMER HOMOPOLYMER TYPE C; AMINOMETHYL PROPANEDIOL; ALOE VERA LEAF; ALPHA-TOCOPHEROL ACETATE

Drug Facts

Uses

- For hand washing to decrease bacteria on the skin.
- Recommended for repeated use.
- Dries in seconds

Warnings

- Flammable, keep away from fire or flame.
- For external use only.
- Do not use in or contact the eyes.
- Discontinue use if irritation and redness develop. If condition persist for more than 72 hours consult a physician.
- If swallowed, get medical help or contact a Poison Control Center immediately.

KEEP OUT OF REACH OF CHILDREN

- Keep this out of reach of children unless under adult supervision.

Directions

- To start feed: Remove cover and discard seal from container. From center of wipe roll, pull up wipe corner; tear off first wipe for use. Twist next wipe into a point and thread through the hole in the container cover. Pull through about one inch. Replace cover. Pull out wipes as needed and snap off at 90o angle. Keep center cap closed to prevent moisture loss.
- Wipe hands, fingers, interdigital areas and wrists thoroughly with towelette. Be sure to utilize the entire wipe surface. Allow to dry.
- For dirty hands, use first wipe to clean hands, then discard wipe; sanitize with second wipe.
- Discard after single use.

Other information

Lot No. and Expiration Date can be found on canister

Dosage

For dirty hands, use first wipe to clean hands, then discard wipe; sanitize with second wipe. Discard after single use.

Inactive ingredients

Water, Propylene Glycol, Glycerin, Carbomer, Aminometyl Propanol, Aloe Barbadensis Leaf Juice, Tocopheryl Acetate

Professional Disposables International, Inc.
Orangeburg, NY 10962-1376 - USA - 1-800-999-6423
www.saniprofessional.com

Principal Display Panel - 150 Count Canister

Sani

Professional(R)

Brand

SANI-HANDS(R)

#1 Handwipe in Healthcare

- Kills 99.99% of Germs
- Removes Soil and Bacteria More Effectively Than Gels Alone
- Contains Moisturizing Aloe and Vitamin E

50
Instant Hand Sanitizing Wipes
6.0 x 6.75 in (15.24 x 17.14 cm)

Front Canister Label
Back Canister Label

Active ingredient

Alcohol 65.9% by volume

Purpose

Antiseptic